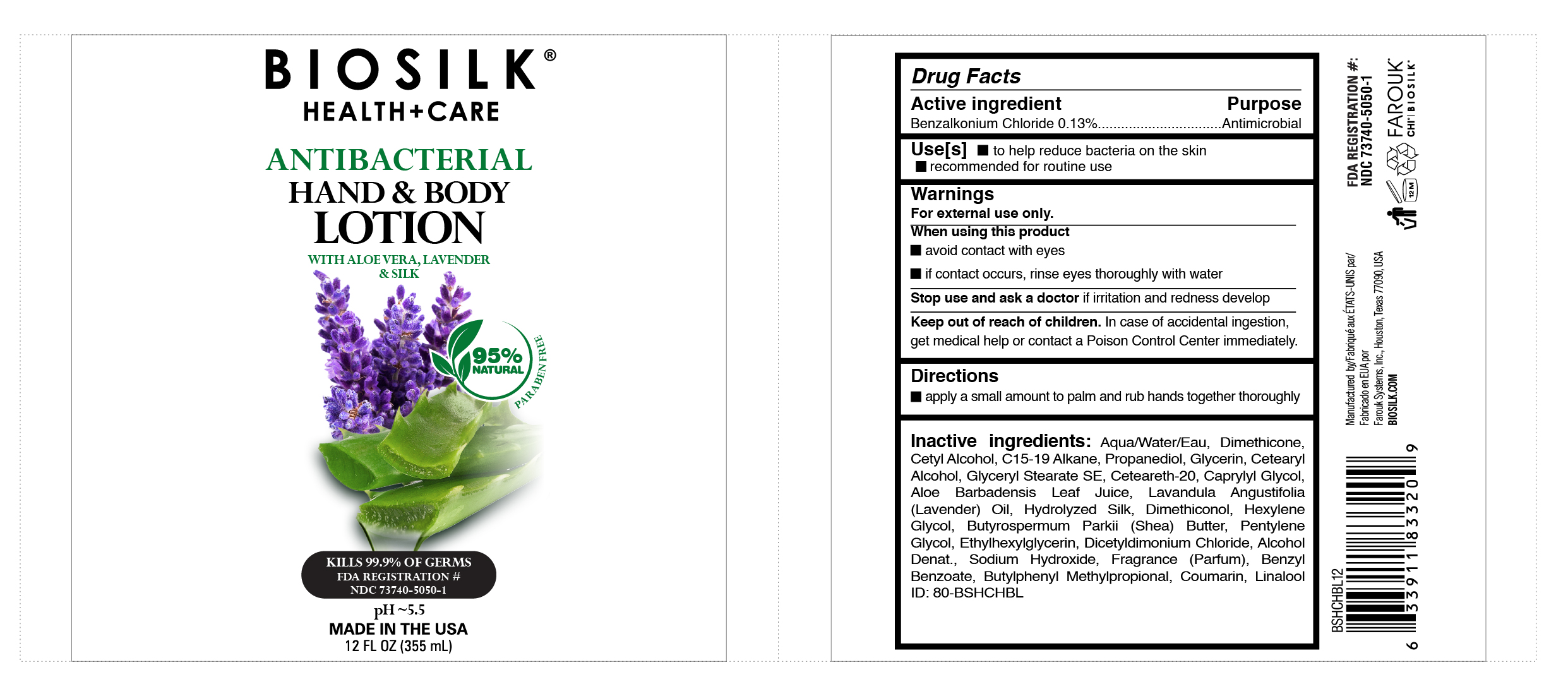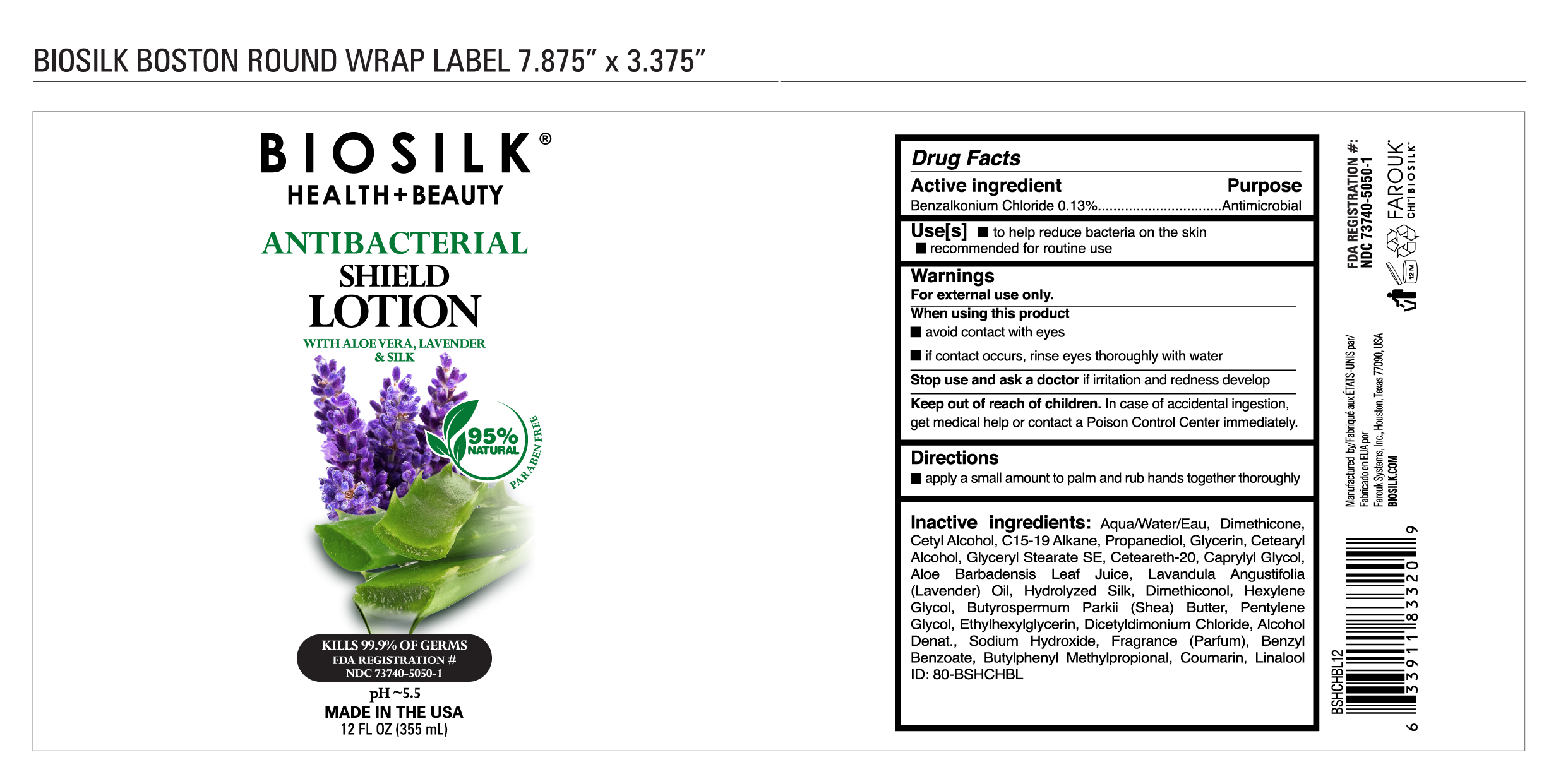 DRUG LABEL: Biosilk
NDC: 73740-5050 | Form: LOTION
Manufacturer: Farouk Systems, Inc.
Category: otc | Type: HUMAN OTC DRUG LABEL
Date: 20200908

ACTIVE INGREDIENTS: BENZALKONIUM 0.13 g/100 g
INACTIVE INGREDIENTS: SILK, ACID HYDROLYZED (1000 MW) 0.01 g/100 g; PENTYLENE GLYCOL 0.3 g/100 g; ETHYLHEXYLGLYCERIN 0.2 g/100 g; SODIUM HYDROXIDE 0.00065 g/100 g; LINALOOL, (+/-)- 0.012 g/100 g; GLYCERIN 2 g/100 g; LAVENDER OIL 0.05 g/100 g; BENZYL BENZOATE 0.2 g/100 g; BUTYLPHENYL METHYLPROPIONAL 0.03 g/100 g; COUMARIN 0.016 g/100 g; CETOSTEARYL ALCOHOL 1.9 g/100 g; POLYOXYL 20 CETOSTEARYL ETHER 1.4 g/100 g; C15-19 ALKANE 3 g/100 g; WATER 76.25635 g/100 g; DIMETHICONE 4.72 g/100 g; DIMETHICONOL (100000 CST) 0.48 g/100 g; DICETYLDIMONIUM CHLORIDE 0.14 g/100 g; ALCOHOL 0.011 g/100 g; FRAGRANCE LAVENDER & CHIA F-153480 0.142 g/100 g; CETYL ALCOHOL 3.8 g/100 g; GLYCERYL STEARATE SE 1.4 g/100 g; CAPRYLYL GLYCOL 1 g/100 g; ALOE VERA LEAF 0.001 g/100 g; HEXYLENE GLYCOL 0.4 g/100 g; SHEA BUTTER 0.3 g/100 g; PROPANEDIOL 2.1 g/100 g

Biosilk Health Plus Beauty Lotion

Active Ingredient

Active ingredient Purpose
Benzalkonium Chloride 0.13%................................Antimicrobial

Inactive ingredients

Inactive ingredients: Aqua/Water/Eau, Dimethicone,
Cetyl Alcohol, C15-19 Alkane, Propanediol, Glycerin, Cetearyl
Alcohol, Glyceryl Stearate SE, Ceteareth-20, Caprylyl Glycol,
Aloe Barbadensis Leaf Juice, Lavandula Angustifolia
(Lavender) Oil, Hydrolyzed Silk, Dimethiconol, Hexylene
Glycol, Butyrospermum Parkii (Shea) Butter, Pentylene
Glycol, Ethylhexylglycerin, Dicetyldimonium Chloride, Alcohol
Denat., Sodium Hydroxide, Fragrance (Parfum), Benzyl
Benzoate, Butylphenyl Methylpropional, Coumarin, Linalool

Keep out of reach of children. In case of accidental ingestion,
get medical help or contact a Poison Control Center immediately.

Purpose

Use[s] to help reduce bacteria on the skin
recommended for routine use

Uses

Use[s] to help reduce bacteria on the skin
recommended for routine use

Warnings

For external use only.
When using this product
avoid contact with eyes
if contact occurs, rinse eyes thoroughly with water
Stop use and ask a doctor if irritation and redness develop
Keep out of reach of children. In case of accidental ingestion,
get medical help or contact a Poison Control Center immediately.

Directions

apply a small amount to palm and rub hands together thoroughly

Primary Display Panel

Biosilk

Health + Care

Antibacterial

Hand & Body

Lotion

with aloe vera, lavender & silk

95% Natural Paraben Free

Kills 99.9% of Germs

FDA Registration #

NDC 73740-5050-1